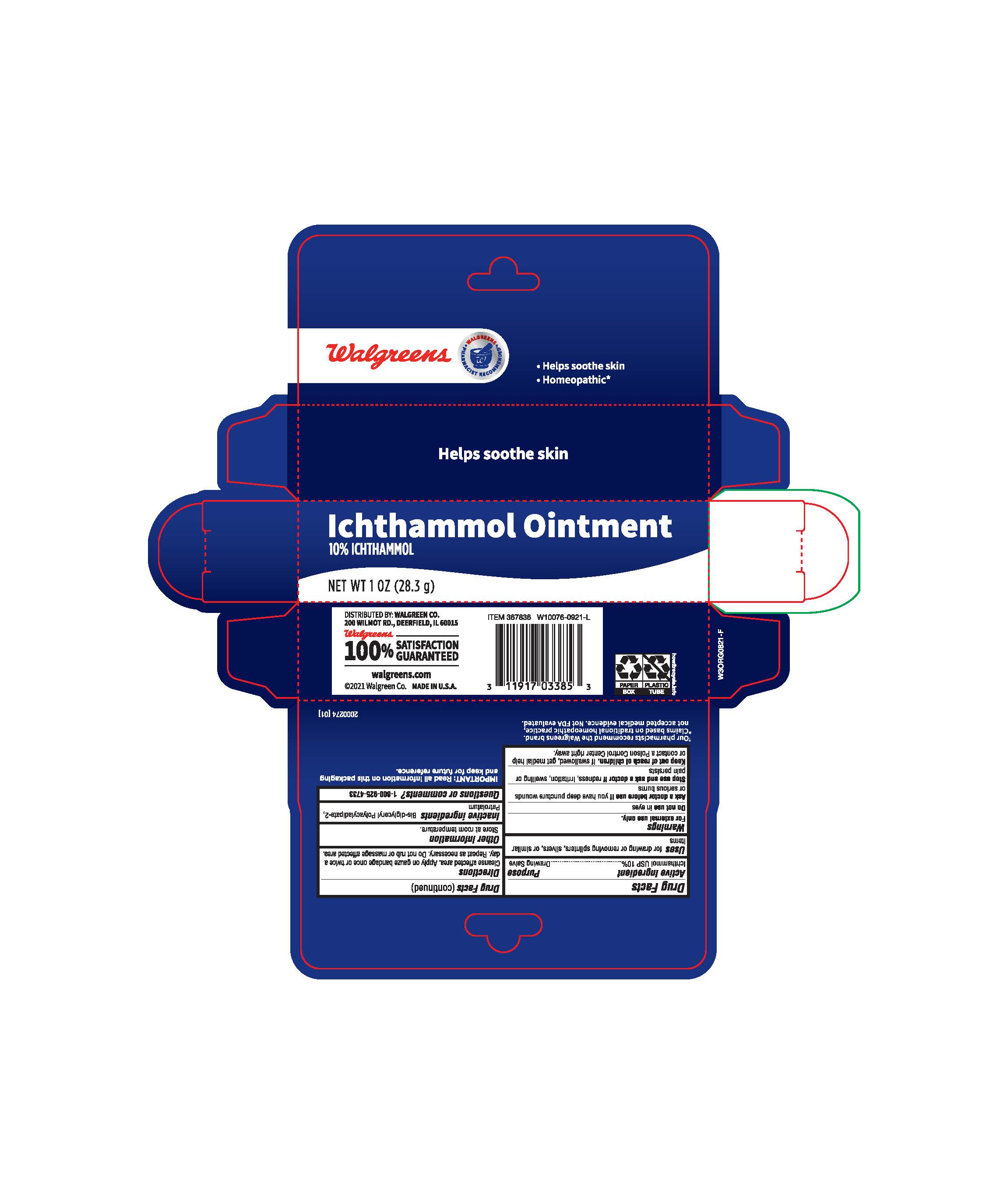 DRUG LABEL: Ichthammol
NDC: 0363-2052 | Form: OINTMENT
Manufacturer: Walgreens
Category: otc | Type: HUMAN OTC DRUG LABEL
Date: 20231031

ACTIVE INGREDIENTS: ICHTHAMMOL 100 mg/1 g
INACTIVE INGREDIENTS: PETROLATUM; BIS-DIGLYCERYL POLYACYLADIPATE-2

Walgreens Ichthammol Ointment

Active Ingredient

Ichthammol USP 10%

Purpose

Drawing Salve

Uses

for drawing or removing splinters, silvers, or similar items.

Warnings

For external use only

Do not use

in eyes

Ask a doctor before use

if you have deep puncture wounds or serious burns

Stop use and ask doctor if

redness, irritation, swelling or pain persists.

Keep out of reach of children

If swallowed, get medical help or contact a Poison Control Center right away.

Directions

Cleanse affected area. Apply on gauze bandage once or twice a day. Repeat as necessary. Do not rub or massage affected area.

Other information

Store at room temperature.

Inactive ingredients

Bis-diglyceryl Polyacyladipate-2, Petrolatum

Questions or comments?

1-800-925-4733